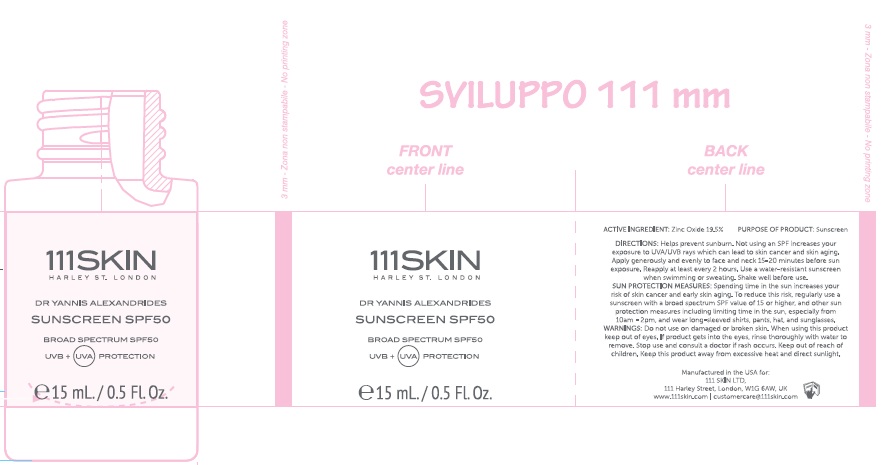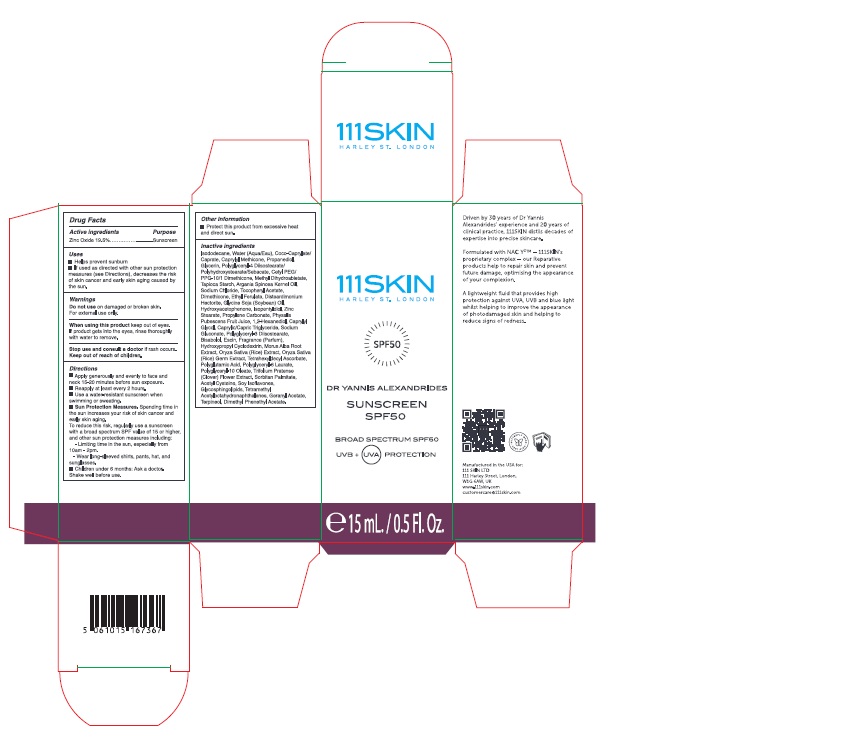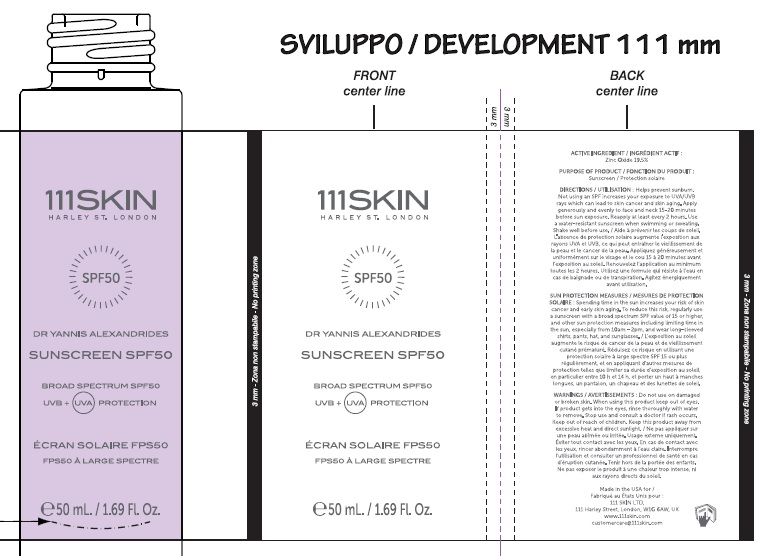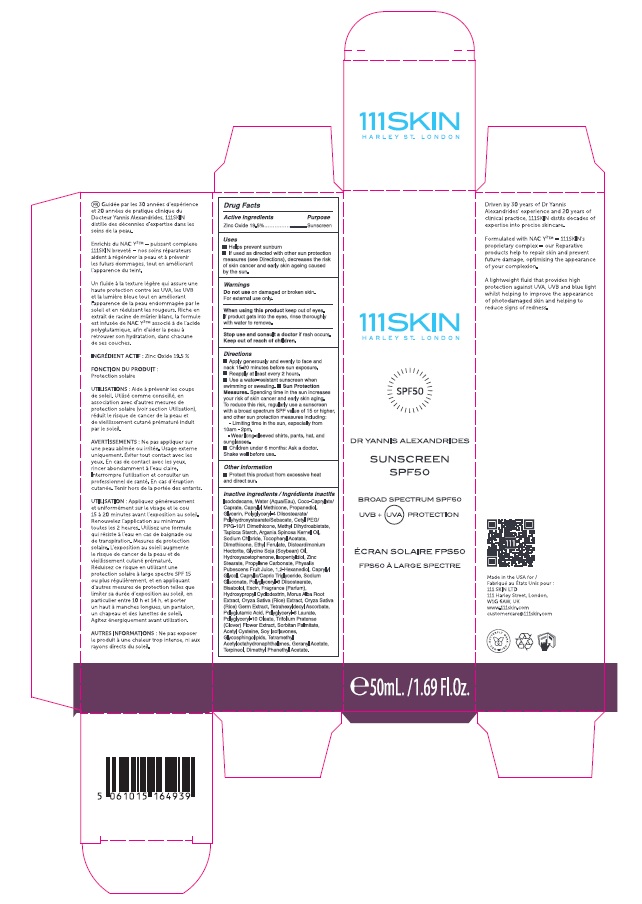 DRUG LABEL: 111 SKIN SUNSCREEN SPF 50
NDC: 54111-190 | Form: SOLUTION
Manufacturer: Bentley Laboratories, LLC
Category: otc | Type: HUMAN OTC DRUG LABEL
Date: 20260123

ACTIVE INGREDIENTS: ZINC OXIDE 19.5 g/100 mL
INACTIVE INGREDIENTS: ISODODECANE; WATER; COCO-CAPRYLATE/CAPRATE; CAPRYLYL METHICONE; PROPANEDIOL; GLYCERIN; POLYGLYCERYL-4 DIISOSTEARATE/POLYHYDROXYSTEARATE/SEBACATE; CETYL PEG/PPG-10/1 DIMETHICONE (HLB 2); METHYL DIHYDROABIETATE; TAPIOCA STARCH; ARGANIA SPINOSA KERNEL OIL; SODIUM CHLORIDE; .ALPHA.-TOCOPHEROL ACETATE; DIMETHICONE; ETHYL FERULATE; DISTEARDIMONIUM HECTORITE; GLYCINE SOJA (SOYBEAN) OIL UNSAPONIFIABLES; HYDROXYACETOPHENONE; ISOPENTYLDIOL; ZINC STEARATE; PROPYLENE CARBONATE; PHYSALIS PUBESCENS FRUIT JUICE; 1,2-HEXANEDIOL; CAPRYLYL GLYCOL; CAPRYLIC/CAPRIC TRIGLYCERIDE; SODIUM GLUCONATE; POLYGLYCERYL-3 DIISOSTEARATE; BISABOLOL; ESCIN; HYDROXYPROPYL BETADEX; MORUS ALBA ROOT; RICE GERM; RICE GERM OIL; TETRAHEXYLDECYL ASCORBATE; POLYGLUTAMIC ACID (1200 MW); POLYGLYCERYL-6 LAURATE; POLYGLYCERYL-10 OLEATE; TRIFOLIUM PRATENSE FLOWER; SORBITAN PALMITATE; ACETYL CYSTEINE; SOY ISOFLAVONES; HYDROXYETHYL PALMITYL OXYHYDROXYPROPYL PALMITAMIDE; TETRAMETHYL ACETYLOCTAHYDRONAPHTHALENES; GERANYL ACETATE; TERPINEOL; DIMETHYL BENZYL CARBINYL ACETATE

111 SKIN SUNSCREEN SPF 50

Drug Facts

Active Ingredients

Zinc Oxide 19.5%

Purpose

Sunscreen

Uses

- Helps prevent sunburn

- If used as directed with other sun protection

measures (see Directions), decreases the risk

of skin cancer and early aging caused

by the sun.

Warnings

Do not use on damaged or broken skin.

For external use only.

When using this product keep out of eyes.

If product gets into the eyes, rinse with water to remove

Stop use and consult a doctor if rash occurs.

Keep out of reach of children.

Directions
• Apply generously and evenly to face and
neck 15-20 minutes before sun exposure.
• Reapply at least every 2 hours
• Use a water-resistant sunscreen when
swimming or sweating. • Sun Protection
Measures. Spending time in the sun increases
your risk of skin cancer and early aging.
To reduce this risk, regularly use a sunscreen
with a Broad Spectrum SPF value of 15 or higher
and other sun protection measures including:
- Limiting time in the sun, especially from 10 a.m. - 2 p.m.
- Wear long-sleeved shirts, pants, hats, and sunglasses.
• Children under 6 months: Ask a doctor.

Other Information

- Protect this product from excessive heat and direct sun.

Inactive ingredients/Ingredients inactifs
Isododecane, Water (Aqua/Eau), Coco-Caprylate/
Caprate, Caprylyl Methicone, Propanediol,
Glycerin, Polyglyceryl-4 Diisostearate/
Polyhydroxystearate/Sebacate, Cetyl PEG/
PPG-10/1 Dimethicone, Methyl Dihydroabietate,
Tapioca Starch, Argania Spinosa Kernel Oil,
Sodium Chloride, Tocopheryl Acetate,
Dimethicone, Ethyl Ferulate, Disteardimonium
Hectorite, Glycine Soja (Soybean) Oil,
Hydroxyacetophenone, Isopentyldiol, Zinc
Stearate, Propylene Carbonate, Physales
Pubescens Fruit Juice, 1,2-Hexanediol, Caprylyl
Glycol, Caprylic/Capric Triglyceride, Sodium
Gluconate, Polyglyceryl-3 Diisostearate,
Bisabolol, Escin, Fragrance (Parfum),
Hydroxypropyl Cyclodextrin, Morus Alba Root
Extract, Oryza Sativa (Rice) Extract, Oryza Sativa
(Rice) Germ Extract, Tetrahexyldecyl Ascorbate,
Polyglutamic Acid, Polyglyceryl-6 Laurate,
Polycglyceryl-10 Oleate, Trifolium Pratense
(Clover) Flower Extract Sorbitan Palmitate,
Acetyl Cysteine, Soy Isoflavones,
Glycosphingolipids, Tetramethyl
Acetyloctahydronaphthalenes, Geranyl Acetate,
Terpineol, Dimethyl Phenethyl Acetate.

Product Labeling: 111 SKIN SUNSCREEN SPF 50

111SKIN

HARLEY ST. LONDON

SPF 50

DR YANNIS ALEXANDRIDES

SUNSCREEN

SPF50

℮50mL./1.69 Fl.Oz.

Made in the USA for:

111 SKIN LTD

111 Harley Street, London,

WiG 6AW, UK

www.111skin@111skin.com

50 mL Carton

50 mL Bottle

15 mL Carton

15 mL Bottle

res